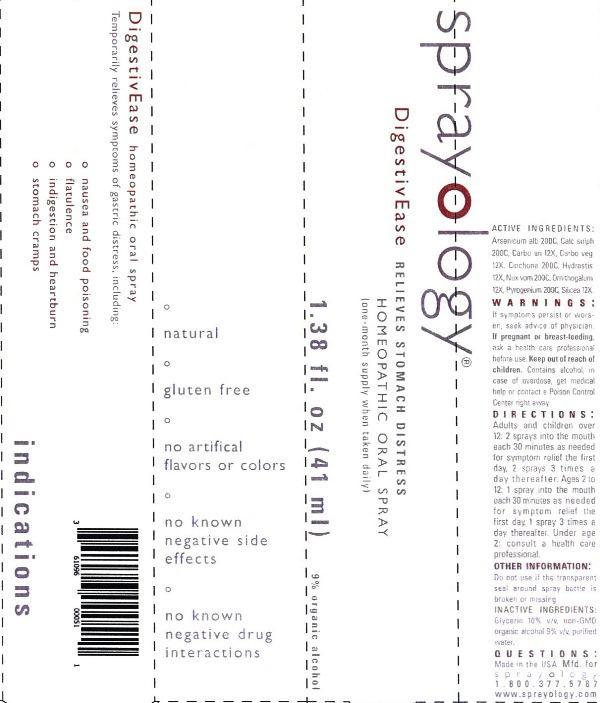 DRUG LABEL: Sprayology DigestivEase
NDC: 61096-0005 | Form: LIQUID
Manufacturer: Eight and Company
Category: homeopathic | Type: HUMAN OTC DRUG LABEL
Date: 20140317

ACTIVE INGREDIENTS: ARSENIC TRIOXIDE 200 [hp_C]/41 mL; CALCIUM SULFATE ANHYDROUS 200 [hp_C]/41 mL; CARBO ANIMALIS 12 [hp_X]/41 mL; ACTIVATED CHARCOAL 12 [hp_X]/41 mL; CINCHONA OFFICINALIS BARK 200 [hp_C]/41 mL; GOLDENSEAL 12 [hp_X]/41 mL; STRYCHNOS NUX-VOMICA SEED 200 [hp_C]/41 mL; ORNITHOGALUM UMBELLATUM 12 [hp_X]/41 mL; RANCID BEEF 200 [hp_C]/41 mL; SILICON DIOXIDE 12 [hp_X]/41 mL
INACTIVE INGREDIENTS: GLYCERIN; ALCOHOL; WATER

Sprayology DigestivEase

ACTIVE INGREDIENT

Active Ingredients: Arsenicum album 200C, Calcarea sulphurica 200C, Carbo animalis 12X, Carbo vegetabilis 12X, Cinchona officinalis 200C, Hydrastis canadensis 12X, Nox vomica 200C, Ornithogalum 12X, Pyrogenium 200, Silicea 12X

WARNINGS

Warnings: If symptoms persist or worsen, seek advice of physician. If pregnant or breast-feeding, ask a health care professional before use. Keep out of reach of children. Contains alcohol, in case of overdose, get medical help or contact a Poison Control Center right away.

Keep out of reach of children.

Directions:

- Adults and children over 12: 2 sprays into the mouth each 30 minutes as needed for symptom relief the first day, 2 sprays 3 times a day thereafter.
- Ages 2 to 12: 1 spray into the mouth each 30 minutes as needed for symptom relief the first day, 1 spray 3 times a day thereafter. Under age 2: consult a health care professional.

PURPOSE

Temporarily relieves symptoms of gastric distress, including:

- nausea and food poisoning
- flatulence
- indigestion and heartburn
- stomach cramps

Other Information: Do not use if the transparent seal around spray bottle is broken or missing.

INACTIVE INGREDIENT

Inactive Ingredients: Glycerin 10% v/v, non-GMO organic alcohol 9% v/v and purified water.

INDICATIONS AND USAGE

Temporarily relieves symptoms of gastric distress, including:

° nausea and food poisoning

° flatulence

° indigestion and heartburn

° stomach cramps

° natural

° gluten free

° no artificial flavors or colors

° no known negative side effects

° no known negative drug interactions